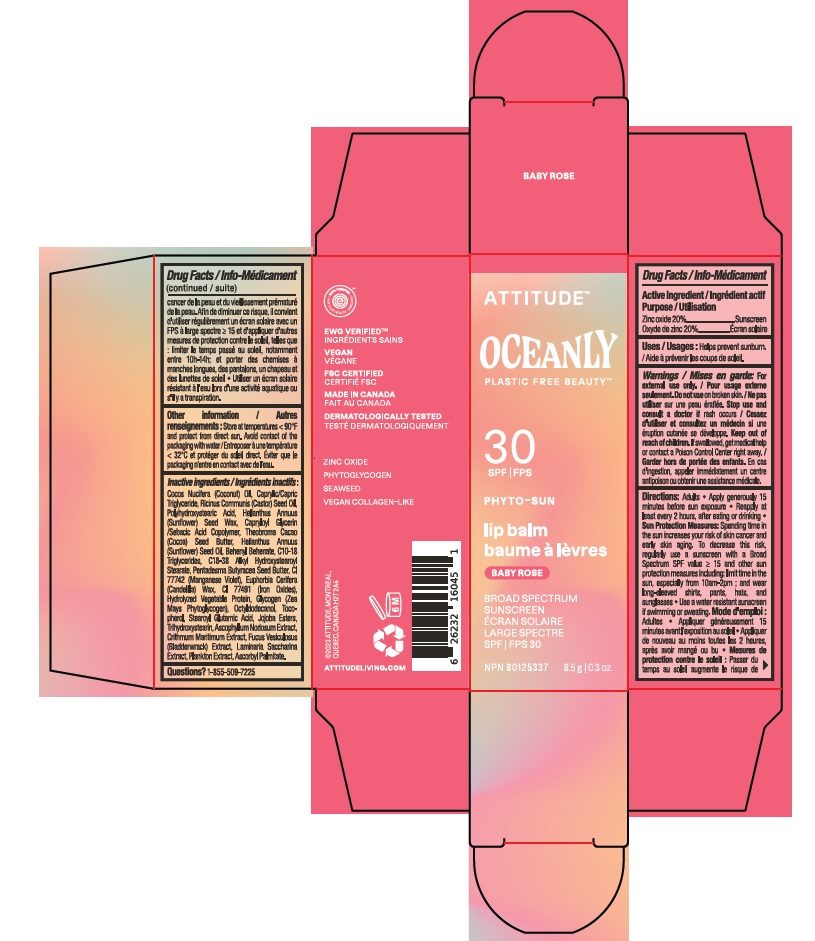 DRUG LABEL: ATTITUDE Oceanly Phyto-sun lip balm SPF 30 Baby Rose
NDC: 61649-045 | Form: STICK
Manufacturer: 9055-7588 Quebec Inc. DBA Attitude
Category: otc | Type: HUMAN OTC DRUG LABEL
Date: 20251020

ACTIVE INGREDIENTS: ZINC OXIDE 20 g/100 g
INACTIVE INGREDIENTS: TETRASELMIS SUECICA; COCONUT OIL; MEDIUM-CHAIN TRIGLYCERIDES; CASTOR OIL; POLYHYDROXYSTEARIC ACID (2300 MW); HELIANTHUS ANNUUS SEED WAX; CAPRYLOYL GLYCERIN/SEBACIC ACID COPOLYMER (2000 MPA.S); SUNFLOWER OIL; PENTADESMA BUTYRACEA WHOLE; MANGANESE VIOLET; FERRIC OXIDE RED; GLYCOGEN; STEAROYL GLUTAMIC ACID; TRIHYDROXYSTEARIN; ASCOPHYLLUM NODOSUM; CRITHMUM MARITIMUM; FUCUS VESICULOSUS; SACCHARINA LATISSIMA; ASCORBYL PALMITATE; HYDROLYZED WHEAT PROTEIN (ENZYMATIC, 3000 MW); HYDROLYZED SOY PROTEIN (ENZYMATIC; 2000 MW); COCOA BUTTER; C10-18 TRIGLYCERIDES; OCTYLDODECANOL; BEHENYL BEHENATE; C18-38 ALKYL HYDROXYSTEAROYL STEARATE; CANDELILLA WAX; .ALPHA.-TOCOPHEROL; JOJOBA OIL; CORN

ATTITUDE Oceanly Phyto-sun lip balm SPF 30 Baby Rose

DRUG FACTS

ACTIVE INGREDIENT

Zinc oxide (20 %)

PURPOSE

Sunscreen

INDICATIONS AND USAGE

Helps prevent sunburn.

WARNINGS

For external use only.

Do not use on broken skin.

Keep out of reach of children. If swallowed, get medical help or contact a Poison Control Center right away.

Stop use and consult a doctor if rash occurs.

DOSAGE AND ADMINISTRATION

Adults.

- Apply generously 15 minutes before sun exposure.
- Reapply at least every 2 hours, after eating or drinking.
- Sun Protection Measures: Spending time in the sun increases your risk of skin cancer and early aging. To decrease this risk, regularly use a sunscreen with a Broad Spectrum SPFvalue of 15 or higher and other sun protection measures including: limit time in the sun, especially from 10am-2pm; and wear long-sleeved shirts, pants, hats and sunglasses.
- Use a water resistant sunscreen if swimming or sweating.

INACTIVE INGREDIENT

Cocos Nucifera (Coconut) Oil, Caprylic/Capric Triglyceride, Ricinus Communis (Castor) Seed Oil, Polyhydroxystearic Acid, Helianthus Annuus (Sunflower) Seed Wax, Capryloyl Glycerin/Sebacic Acid Copolymer, Theobroma Cacao (Cocoa) Seed Butter, Helianthus Annuus (Sunflower) Seed Oil, Behenyl Behenate, C10-18 Triglycerides, C18-38 Alkyl Hydroxystearoyl Stearate, Pentadesma Butyracea Seed Butter, CI 77742 (Manganese Violet), Euphorbia Cerifera (Candelilla) Wax, CI 77491 (Iron Oxides), Hydrolyzed Vegetable Protein, Glycogen (Zea Mays Phytoglycogen), Octyldodecanol, Tocopherol, Stearoyl Glutamic Acid, Jojoba Esters, Trihydroxystearin, Ascophyllum Nodosum Extract, Crithmum Maritimum Extract, Fucus Vesiculosus (Bladderwrack) Extract, Laminaria Saccharina Extract, Plankton Extract, Ascorbyl Palmitate.

STORAGE AND HANDLING

Store at temperatures < 90F and protect from direct sun. Avoid contact of packaging with water.

Questions ? 1-855-509-7225

PACKAGE LABEL

ATTITUDETM

OCEANLY PLASTIC FREE BEAUTYTM

SPF 30

PHYTO-SUN

Lip balm

Baby rose

Broad spectrum sunscreen

Zinc oxide

Phytoglycogen

Seaweed

Vegan Collagen-like

NPN 80125337

8.5 g / 0.3 oz.

EWG Verified

Vegan

FSC Certified

Made in Canada

Dermatologically tested